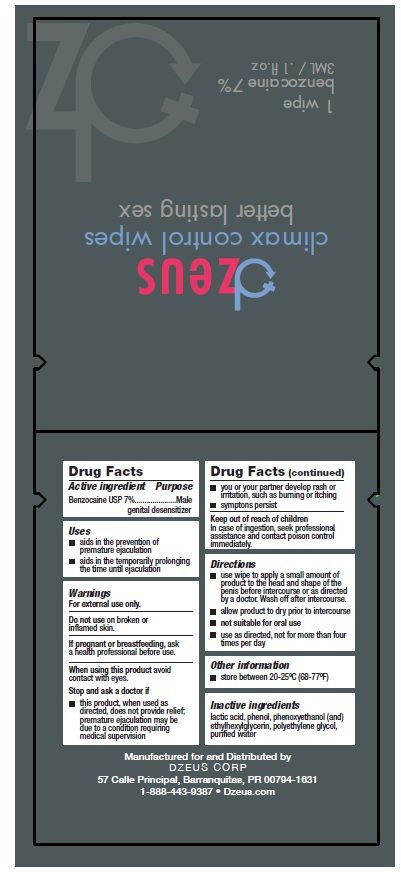 DRUG LABEL: DZEUS Climax control wipes
NDC: 54723-006 | Form: CLOTH
Manufacturer: Sambria Pharmaceuticals, LLC
Category: otc | Type: HUMAN OTC DRUG LABEL
Date: 20240117

ACTIVE INGREDIENTS: BENZOCAINE 7 g/100 mL
INACTIVE INGREDIENTS: WATER; LACTIC ACID, UNSPECIFIED FORM; PHENOL; PHENOXYETHANOL; ETHYLHEXYLGLYCERIN; POLYETHYLENE GLYCOL, UNSPECIFIED

Active ingredient

Benzocaine USP 7%

Purpose

Male genital desensitizer

Uses

- Aids in the prevention of premature ejaculation
- Aids in temporarily prolonging the time until ejaculation

Warnings

For External Use only.
Do not use onbroken or inflamed skin.
If pregnant or breastfeeding, ask a health professional before use.
When using thisproduct, avoid contact with eyes.
Stop and ask doctor if:
This product, when used as directed, does not provide relief; premature ejaculation may be due to a condition requiring medical supervision,you or your partner develop rash or irritation, such as burning or itching symptoms persist.

Keep out of reach of children

In case of ingestion, seek professional assistance and contact poison control immediately.

Directions

Use wipe to apply a small amount of product to the head and shape of the penis before intercourse, or as directed by a doctor. Wash off after intercourse.
Allow product to dry prior to intercourse.
Not suitable for oral use.
Use as directed.

Other information

Store between 20°-25 °C (68°-77 °F)

Inactive ingredients

Lactic Acid, Phenol, Phenoxyethanol, ethylhexylglycerin, Polyethylene Glycol, purified water